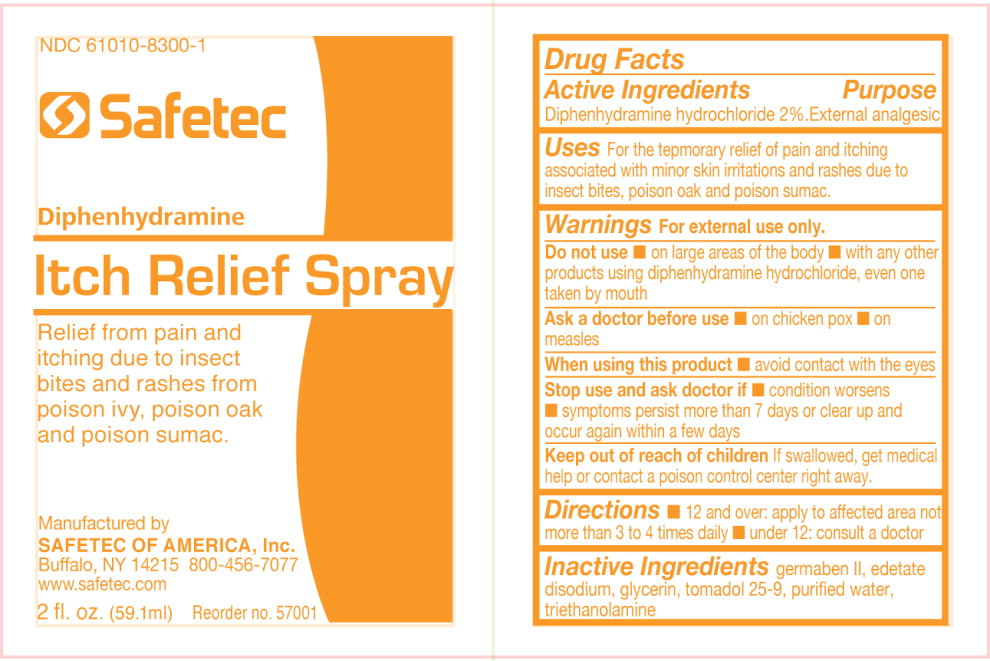 DRUG LABEL: Itch Relief
NDC: 61010-8300 | Form: LIQUID
Manufacturer: Safetec of America, Inc.
Category: otc | Type: HUMAN OTC DRUG LABEL
Date: 20240204

ACTIVE INGREDIENTS: DIPHENHYDRAMINE HYDROCHLORIDE 20.3 g/1 L
INACTIVE INGREDIENTS: DIAZOLIDINYL UREA; EDETATE DISODIUM; GLYCERIN; C12-15 PARETH-9; WATER; TROLAMINE

61010-8300, Itch Relief Spray

Drug Facts

Active Ingredients

Diphenhydramine hydrochloride 2%

Purpose

External Analgesic

Uses:

For the temporary relief of pain and itching associated with minor skin irritations and rashes due to insect bites, poison oak and poison sumac.

Warnings

For external use only

Do not use

- on large areas of the body
- with any other products using diphenhydramine hydrochloride, even one taken by mouth

Ask a doctor before use

- on chicken pox
- on measles

When using this product

- avoid contact with the eyes

Stop use and ask doctor if

- condition worsens
- symptoms persist more than 7 days or clear up and occur again within a few days

KEEP OUT OF REACH OF CHILDREN

Keep out of reach of childrenIf swallowed, get medical help or contact a poison control center right away.

Directions:

- 12 and over: apply to affected area not more than 3 to 4 times daily
- under 12: consult a doctor

Inactive Ingredients:

Germaben II, edetate disodium, glycerin, tomadol 25-9, purified water, triethanolamine

PRINCIPAL DISPLAY PANEL

NDC 61010-8300-1

Safetec

Diphenhydramine

Itch Relief Spray

Relief from pain and

itching due to insect

bites and rashes from

poison ivy, poison oak

and poison sumac.

Manufactured by

SAFETEC OF AMERICA, Inc.

Buffalo, NY 14215 800-456-7077

www.safetec.com

2 fl. oz. (59.1ml) Reorder no. 57001